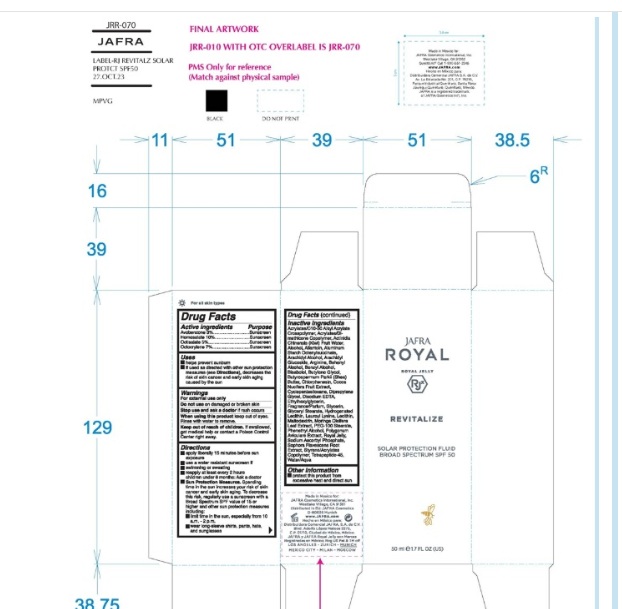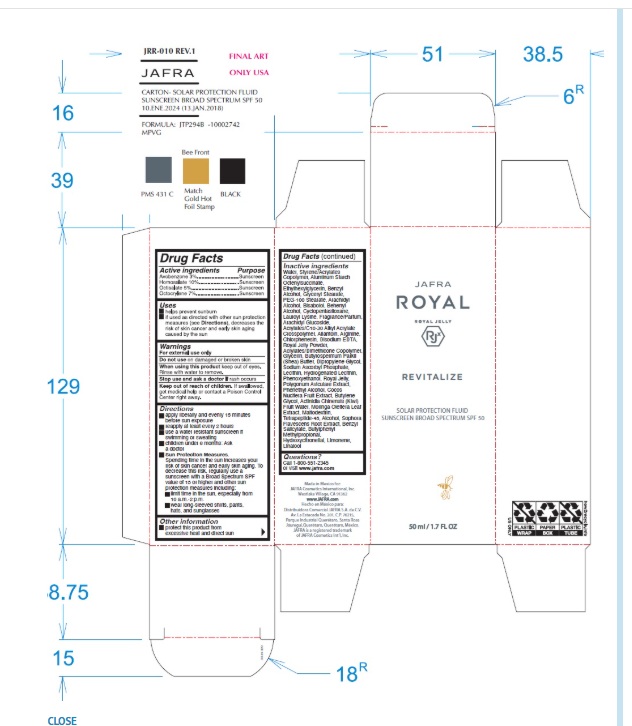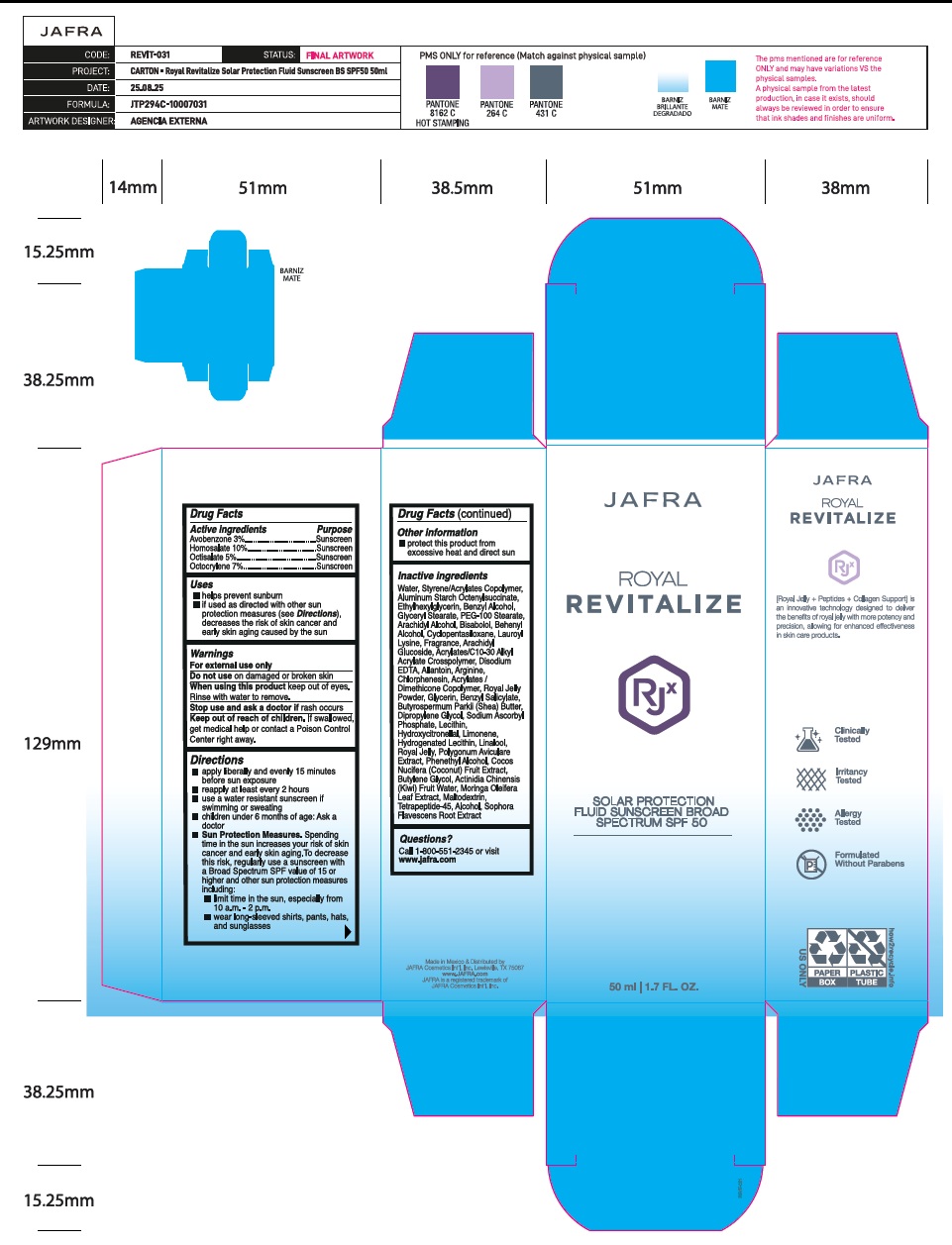 DRUG LABEL: Revitalize Solar Protection Fluid Broad Spectrum SPF 50
NDC: 68828-515 | Form: CREAM
Manufacturer: Distribuidora Comercial Jafra, S.A. de C.V.
Category: otc | Type: HUMAN OTC DRUG LABEL
Date: 20251105

ACTIVE INGREDIENTS: AVOBENZONE 3 g/100 mL; HOMOSALATE 10 g/100 mL; OCTISALATE 5 g/100 mL; OCTOCRYLENE 7 g/100 mL
INACTIVE INGREDIENTS: CARBOMER COPOLYMER TYPE B (ALLYL PENTAERYTHRITOL CROSSLINKED); KIWI FRUIT OIL; ALCOHOL; ALLANTOIN; ALUMINUM STARCH OCTENYLSUCCINATE; ARACHIDYL ALCOHOL; ARACHIDYL GLUCOSIDE; ARGININE; DOCOSANOL; BENZYL ALCOHOL; LEVOMENOL; BUTYLENE GLYCOL; SHEA BUTTER; CHLORPHENESIN; COCONUT; CYCLOMETHICONE 5; DIPROPYLENE GLYCOL; EDETATE DISODIUM; ETHYLHEXYLGLYCERIN; GLYCERIN; GLYCERYL MONOSTEARATE; HYDROGENATED SOYBEAN LECITHIN; LAUROYL LYSINE; LECITHIN, SOYBEAN; MALTODEXTRIN; MORINGA OLEIFERA LEAF; PEG-100 STEARATE; PHENYLETHYL ALCOHOL; POLYGONUM AVICULARE TOP; ROYAL JELLY; SODIUM ASCORBYL PHOSPHATE; SOPHORA FLAVESCENS ROOT; WATER; BENZYL SALICYLATE; HYDROXYCITRONELLAL; LIMONENE, (+)-; LINALOOL, (+/-)-; 2-ETHYLHEXYL ACRYLATE, METHACRYLATE, METHYL METHACRYLATE, OR BUTYL METHACRYLATE/HYDROXYPROPYL DIMETHICONE COPOLYMER (30000-300000 MW)

Active Ingredients

Avobenzone 3%

Homosalate 10%

Octisalate 5%

Octocrylene 7%

Purpose

Sunscreen

Uses

- Helps prevent sunburn
- If used as directed with other sun protection measures (see Directions), decreases the risk of skin cancer and early skin aging caused by the sun.

Warnings

For external use only

Do not use on damaged or broken skin

When using this product keep out of eyes. Rinse with water to remove.

Stop use and ask a doctor if rash occurs

Keep out of reach of children. If swallowed, get medical help or contact a Poison Control Center right away.

Directions

- apply liberally and evenly 15 minutes before sun exposure
- reapply at least every 2 hours.
- use a water-resistant sunscreen if swimming or sweating
- children under 6 months of age: Ask a doctor
- Sun Protection Measures.Spending time in the sun increases your risk of skin cancer and early skin aging. To decrease this risk, regularly use a sunscreen with a Broad-Spectrum SPF value of 15 or higher and other sun protection measures including:
- limit your time in the sun, especially from 10 a.m. – 2 p.m.
- wear long-sleeved shirts, pants, hats, and sunglasses

Other information

- protect this product from excessive heat and direct sun

Inactive ingredients

Water, Styrene/Acrylates Copolymer, Aluminum Starch Octenylsuccinate, Ethylhexylglycerin, Benzyl Alcohol, Glyceryl Stearate, PEG-100 Stearate, Arachidyl Alcohol, Bisabolol, Behenyl Alcohol, Cyclopentasiloxane, Lauroyl Lysine, Fragrance, Arachidyl Glucoside, Acrylates/C10-30 Alkyl Acrylate Crosspolymer, Disodium EDTA, Allantoin, Arginine, Chlorphenesin, Acrylates/Dimethicone Copolymer, Royal Jelly Powder, Glycerin, Benzyl Salicylate, Butyrospermum Parkii (Shea) Butter, Dipropylene Glycol, Sodium Ascorbyl Phosphate, Lecithin, Hydroxycitronellal, Limonene, Hydrogenated Lecithin, Linalool, Royal Jelly, Polygonum Aviculare Extract, Phenethyl Alcohol, Cocos Nucifera (Coconut) Fruit Extract, Butylene Glycol, Actinidia Chinensis (Kiwi) Fruit Water, Moringa Oleifera Leaf Extract, Maltodextrin, Tetrapeptide-45, Alcohol, Sophora Flavescens Root Extract

Questions?

Call 1-800-551-2345 or visit www.jafra.com